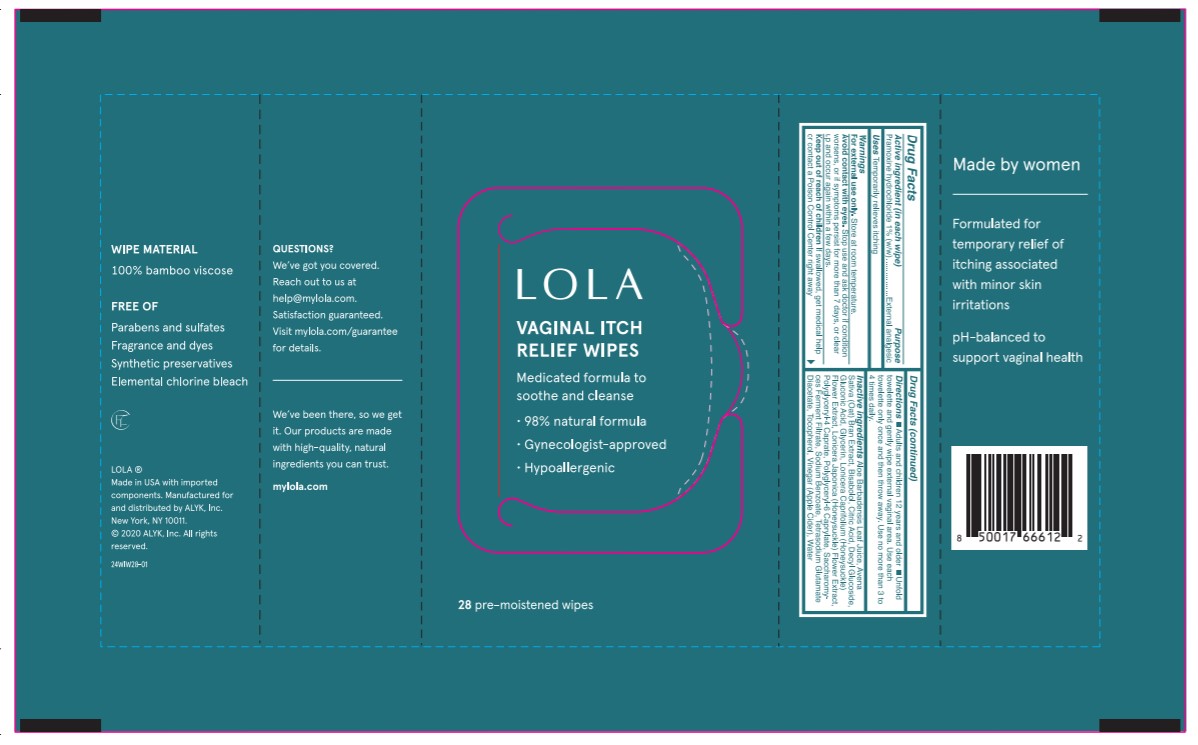 DRUG LABEL: LOLA Vaginal Itch Relief Wipes
NDC: 81032-422 | Form: CLOTH
Manufacturer: Alyk, Inc.
Category: otc | Type: HUMAN OTC DRUG LABEL
Date: 20210407

ACTIVE INGREDIENTS: PRAMOXINE HYDROCHLORIDE 10 mg/1 1
INACTIVE INGREDIENTS: ALOE VERA LEAF; CITRIC ACID MONOHYDRATE; LONICERA JAPONICA FLOWER; SODIUM BENZOATE; TOCOPHEROL; APPLE CIDER VINEGAR; WATER; OAT BRAN; DECYL GLUCOSIDE; GLUCONIC ACID; GLYCERIN; LONICERA CAPRIFOLIUM FLOWER; POLYGLYCERYL-4 CAPRATE; POLYGLYCERYL-6 CAPRYLATE; LEVOMENOL; TETRASODIUM GLUTAMATE DIACETATE

Active Ingredient

Pramoxine hydrochloride 1% (w/w)

Purpose

External analgesic

Use

Temporarily relieves itching

Warnings

For external use only

Avoid contact with eyes

Stop Use

Stop use and ask a doctor if condition worsens, or if symptoms persist for more than 7 days, or clear up and occur again within a few days.

Do Not Use

- Skin: This product is expected to contact with skin. If irritation is experienced, discontinue use of product. If discomfort persists, seek medical attention.
- Eye: Hold eyelid open and flush with water for at least 15 minutes. If irritation persists, seek medical attention.
- Ingestion: Wipes may present a choking hazard. Accidental ingestion may necessitate medical attention.
- Inhalation: Not likely to be inhaled. If symptomatic, remove to fresh air.

Keep out of reach of children. If swallowed, get medical help or contact a Poison Control Center right away.

Directions

Adults and children 12 years and older. Unfold towelette and gently wipe external vaginal area. Use each towelette only once and then throw away. Use no more than 3 to 4 times daily.

Other Information

Use according to package label instructions. Keep in cool storage.

Inactive Ingredient(s)

Aloe Barbadensis Leaf Juice, Avena Sativa (Oat) Bran Extract, Bisabolol, Citric Acid, Decyl Glucoside, Gluconic Acid, Glycerin, Lonicera Caprifolium (Honeysuckle) Flower Extract, Lonicera Japonica (Honeysuckle) Flower Extract, Polyglyceryl-4 Caprate, Polyglyceryl-6 Caprylate, Saccharomyces Ferment Filtrate, Sodium Benzoate, Tetrasodium Glutamate Diacetate, Tocopherol, Vinegar (Apple Cider), Water